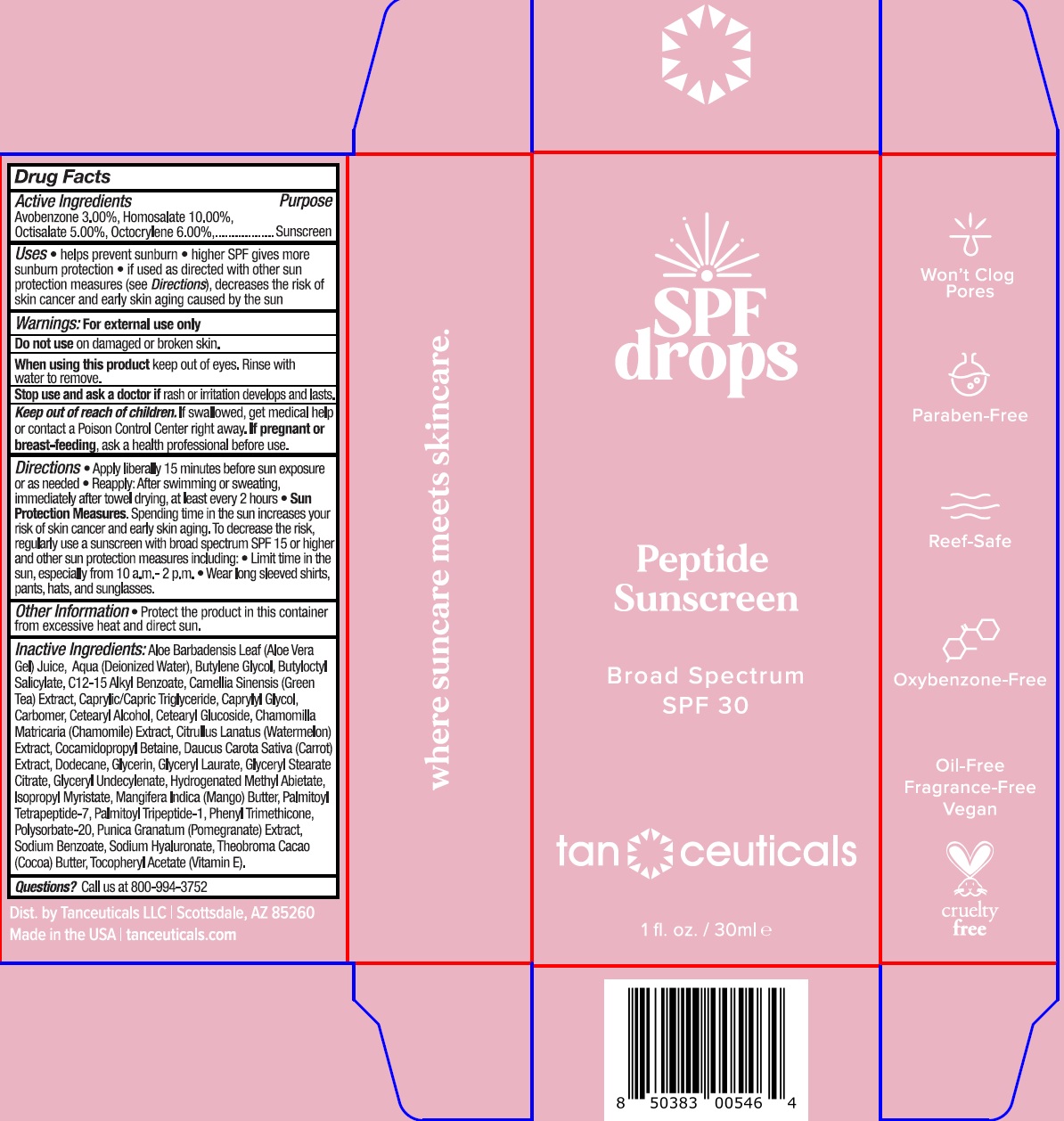 DRUG LABEL: TANCEUTICALS SPF DROPS Broad Spectrum SPF-30
NDC: 82675-279 | Form: SOLUTION
Manufacturer: TANCEUTICALS, LLC
Category: otc | Type: HUMAN OTC DRUG LABEL
Date: 20231111

ACTIVE INGREDIENTS: AVOBENZONE 30 mg/1 mL; HOMOSALATE 100 mg/1 mL; OCTISALATE 50 mg/1 mL; OCTOCRYLENE 60 mg/1 mL
INACTIVE INGREDIENTS: ALOE VERA LEAF; WATER; BUTYLENE GLYCOL; BUTYLOCTYL SALICYLATE; ALKYL (C12-15) BENZOATE; GREEN TEA LEAF; MEDIUM-CHAIN TRIGLYCERIDES; CAPRYLYL GLYCOL; CARBOMER HOMOPOLYMER, UNSPECIFIED TYPE; CETOSTEARYL ALCOHOL; CETEARYL GLUCOSIDE; CHAMOMILE; WATERMELON; COCAMIDOPROPYL BETAINE; CARROT; DODECANE; GLYCERIN; GLYCERYL LAURATE; GLYCERYL STEARATE CITRATE; HYDROGENATED METHYL ABIETATE; ISOPROPYL MYRISTATE; MANGO; PALMITOYL TETRAPEPTIDE-7; PALMITOYL TRIPEPTIDE-1; PHENYL TRIMETHICONE; POLYSORBATE 20; PUNICA GRANATUM ROOT BARK; SODIUM BENZOATE; HYALURONATE SODIUM; COCOA; .ALPHA.-TOCOPHEROL ACETATE

TANCEUTICALS SPF DROPS Broad Spectrum SPF-30

Active Ingredients

Avobenzone 3.00%, Homosalate 10.00%,

Octisalate 5.00%, Octocrylene 6.00%

Purpose

Sunscreen

Uses

- helps prevent sunburn
- higher SPF gives more sunburn protection
- if used as directed with other sun protection measures (see Directions), decreases the risk of skin cancer and early skin aging caused by the sun

Warnings:

For external use only

Do not use

on damaged or broken skin.

When using this product

keep out of eyes. Rinse with water to remove.

Stop use and ask a doctor if

rash or irritation develops and lasts.

Keep out of reach of children.

If swallowed, get medical help or contact a Poison Control Center right away.

If pregnant or breast-feeding,

ask a health professional before use.

Directions

- Apply liberally 15 minutes before sun exposure or as needed
- Reapply:After swimming or sweating, immediately after towel drying, at least every 2 hours
- Spending time in the sun increases your risk of skin cancer and early sking aging. To decrease the risk, regularly use a sunscreen with broad spectrum SPF 15 or higher and other sun protection measures including: Sun Protection Measures.
- Limit time in the sun, especially from 10 a.m.-2 p.m.
- Wear long sleeved shirts, pants, hats, and sunglasses.

Other Information

- Prorect the product in this container from excessive heat and direct sun.

Inactive Ingredients:

Aloe Barbadensis Leaf (Aloe Vera Gel) Juice, Aqua (Deionized Water), Butylene Glycol, Butyloctyl Salicylate, C12-15 Alkyl Benzoate, Camellia Sinensis (Green Tea) Extract, Caprylic/Capric Triglyceride, Caprylyl Glycol, Carbomer, Cetearyl Alcohol, Cetearyl Glucoside, Chamomilla Matricaria (Chamomile) Extract, Citrullus Lanatus (Watermelon) Extract, Cocamidopropyl Betaine, Daucus Carota Sativa (Carrot) Extract, Dodecane, Glycerin, Glyceryl Laurate, Glyceryl Stearate Citrate, Glyceryl Undecylenate, Hydrogenated Methyl Abietate, Isopropyl Myristate, Mangifera Indica (Mango) Butter, Palmitoyl Tetrapeptide-7, Palmitoyl Tripeptide-1, Phenyl Trimethicone, Polysorbate-20, Punica Granatum (Pomegranate) Extract, Sodium Benzoate, Sodium Hyaluronate, Theobroma Cacao (Cocoa) Butter, Tocopheryl Acetate (Vitamin E).

Questions?

Call us at 800-994-3752